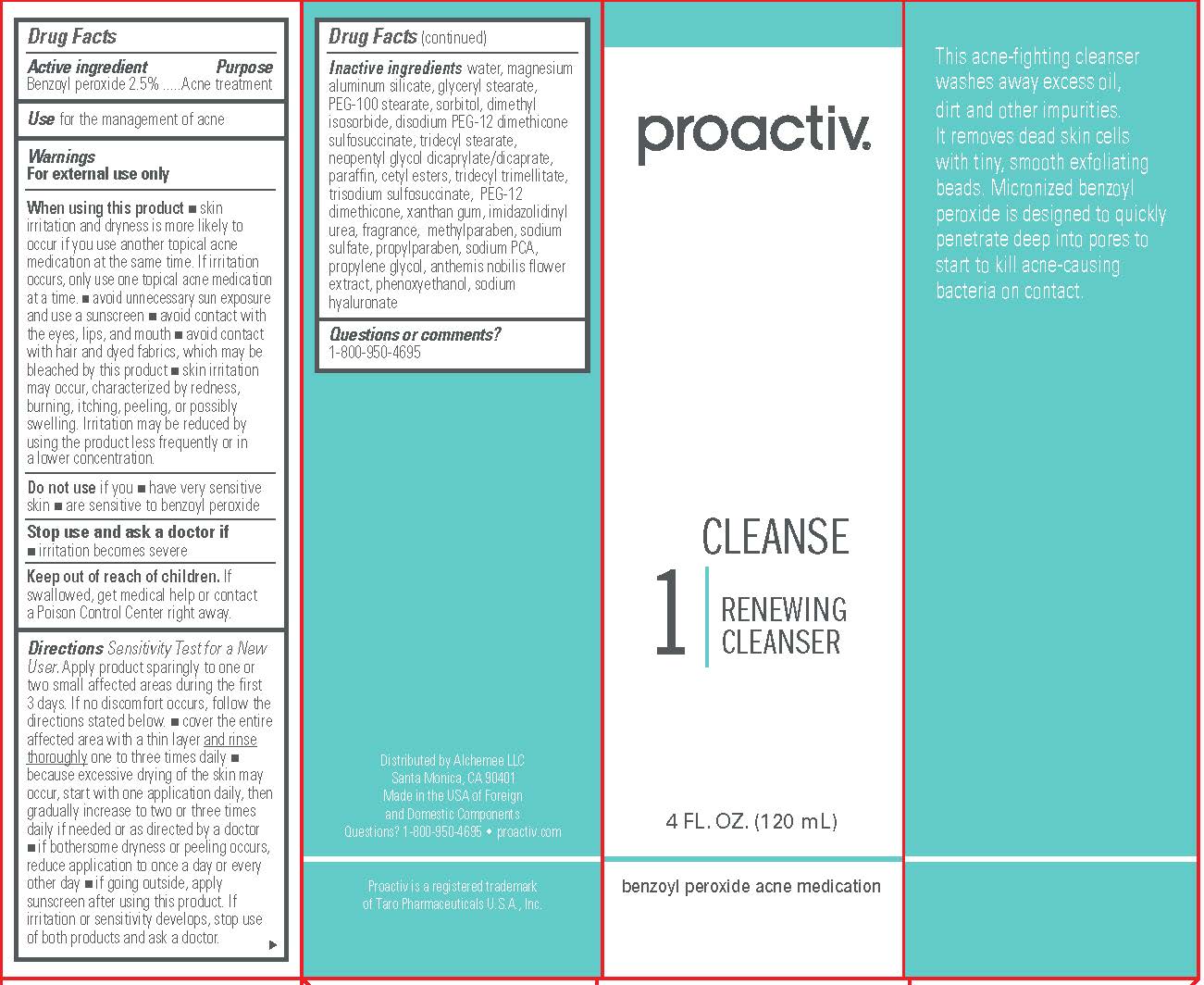 DRUG LABEL: Proactiv Renewing Cleanser
NDC: 11410-005 | Form: GEL
Manufacturer: Alchemee, LLC
Category: otc | Type: HUMAN OTC DRUG LABEL
Date: 20260107

ACTIVE INGREDIENTS: BENZOYL PEROXIDE 2.5 g/100 mL
INACTIVE INGREDIENTS: WATER; MAGNESIUM ALUMINUM SILICATE; GLYCERYL MONOSTEARATE; PEG-100 STEARATE; SORBITOL; DIMETHYL ISOSORBIDE; TRIDECYL STEARATE; NEOPENTYL GLYCOL DICAPRYLATE/DICAPRATE; PARAFFIN; CETYL ESTERS WAX; CHAMAEMELUM NOBILE; TRIDECYL TRIMELLITATE; TRISODIUM SULFOSUCCINATE; PEG-12 DIMETHICONE (300 CST); HYALURONATE SODIUM; PROPYLENE GLYCOL; SODIUM PYRROLIDONE CARBOXYLATE; XANTHAN GUM; PHENOXYETHANOL; METHYLPARABEN; PROPYLPARABEN

Proactiv®Renewing Cleanser

Drug Facts

Active ingredient

Benzoyl peroxide 2.5%

Purpose

Acne treatment

Use

for the management of acne

Warnings

For external use only

When using this product

- skin irritation and dryness is more likely to occur if you use another topical acne medication at the same time. If irritation occurs, only use one topical acne medication at a time.
- avoid unnecessary sun exposure and use a sunscreen.
- avoid contact with the eyes, lips, and mouth.
- avoid contact with hair and dyed fabrics, which may be bleached by this product.
- skin irritation may occur, characterized by redness, burning, itching, peeling, or possibly swelling. Irritation may be reduced by using the product less frequently or in a lower concentration.

Do not useif you

- have very sensitive skin
- are sensitive to benzoyl peroxide

Stop use and ask a doctor if

- irritation becomes severe.

Keep out of reach of children.If swallowed, get medical help or contact a Poison Control Center right away.

Directions

- Sensitivity Test for a New User . Apply product sparingly to one or two small affected areas during the first 3 days. If no discomfort occurs, follow the directions stated below.
- cover the entire affected area with a thin layer and rinse thoroughlyone to three times daily.
- because excessive drying of the skin may occur, start with one application daily, then gradually increase to two or three times daily if needed or as directed by a doctor.
- if bothersome dryness or peeling occurs, reduce application to once a day or every other day.
- if going outside, apply sunscreen after using this product. If irritation or sensitivity develops, stop use of both products and ask a doctor.

Inactive ingredients

water, magnesium aluminum silicate, glyceryl stearate, PEG-100 stearate, sorbitol, dimethyl isosorbide, disodium PEG-12 dimethicone sulfosuccinate, tridecyl stearate, neopentyl glycol dicaprylate/dicaprate, paraffin, cetyl esters, tridecyl trimellitate, trisodium sulfosuccinate, PEG-12 dimethicone, xanthan gum, imidazolidinyl urea, fragrance, methylparaben, sodium sulfate, propylparaben, sodium PCA, propylene glycol, anthemis nobilis flower extract, phenoxyethanol, sodium hyaluronate

Questions or comments?

1-800-950-4695

Distributed by Alchemee LLC
Santa Monica, CA 90401
Made in the USA of Foreign
and Domestic Components
Questions? 1-800-950-4695 • proactiv.com
Proactiv is a registered trademark
of Taro Pharmaceuticals U.S.A., Inc.

PRINCIPAL DISPLAY PANEL - 120 mL CARTON

proactiv®

CLEANSE
1
RENEWING
CLEANSER
4 FL. OZ. (120 mL)
benzoyl peroxide acne medication